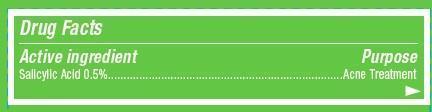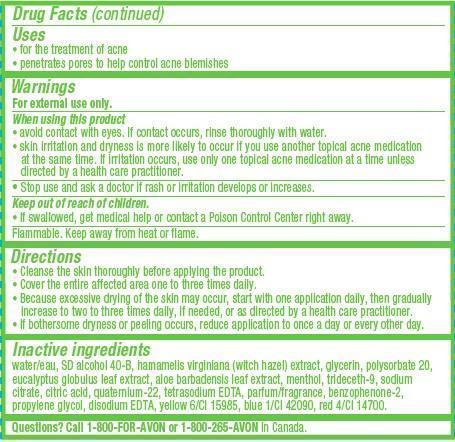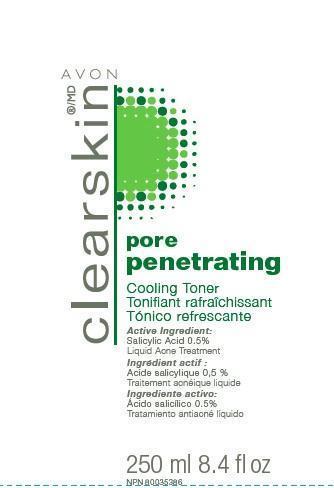 DRUG LABEL: Clearskin Pore Penetrating
NDC: 10096-0289 | Form: LIQUID
Manufacturer: Avon Products, Inc.
Category: otc | Type: HUMAN OTC DRUG LABEL
Date: 20121106

ACTIVE INGREDIENTS: SALICYLIC ACID 5 mg/1 mL

Active ingredient
Salicylic Acid 0.5%.........................................

Purpose
..................................................Acne Treatment

Uses
• for the treatment of acne
• penetrates pores to help control acne blemishes

Warnings
For external use only.

When using this product
• avoid contact with eyes. If contact occurs, rinse thoroughly with water.
• skin irritation and dryness is more likely to occur if you use another topical acne medication at the same time. If irritation occurs, use only one topical acne medication at a time unless directed by a health care practitioner.

• Stop use and ask a doctor if rash or irritation develops or increases.

Keep out of reach of children.
• If swallowed, get medical help or contact a Poison Control Center right away.

STORAGE AND HANDLING

Flammable. Keep away from heat or flame.

Directions
• Cleanse the skin thoroughly before applying the product.
• Cover the entire affected area one to three times daily.
• Because excessive drying of the skin may occur, start with one application daily, then gradually increase to two to three times daily, if needed, or as directed by a health care practitioner.
• If bothersome dryness or peeling occurs, reduce application to once a day or every other day.

Inactive ingredients
water/eau, SD alcohol 40-B, hamamelis virginiana (witch hazel) extract, glycerin, polysorbate 20, eucalyptus globulus leaf extract, aloe barbadensis leaf extract, menthol, trideceth-9, sodium citrate, citric acid, quaternium-22, tetrasodium EDTA, parfum/fragrance, benzophenone-2, propylene glycol, disodium EDTA, yellow 6/CI 15985, blue 1/CI 42090, red 4/CI 14700.

QUESTIONS

Questions? Call 1-800-FOR-AVON or 1-800-265-AVON in Canada.